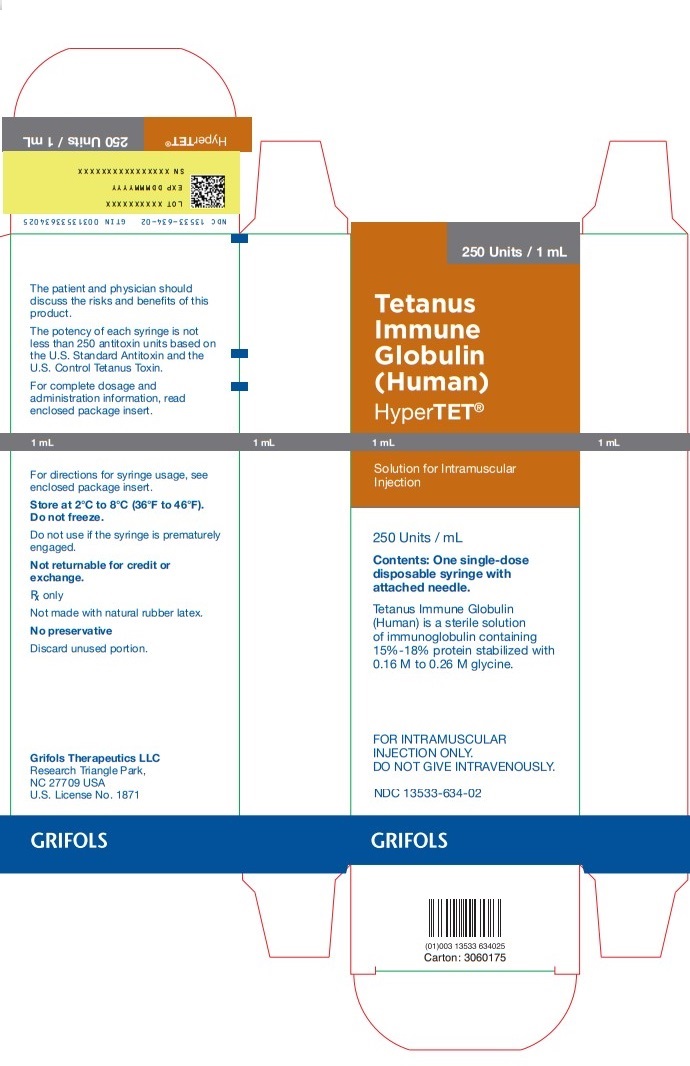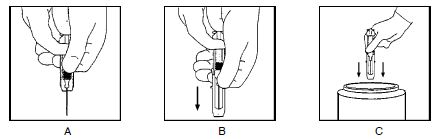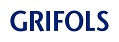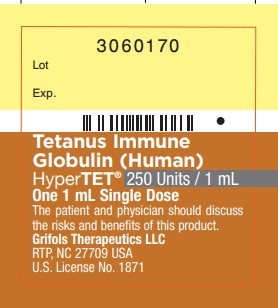 DRUG LABEL: HyperTET
NDC: 13533-634 | Form: INJECTION
Manufacturer: GRIFOLS USA, LLC
Category: other | Type: PLASMA DERIVATIVE
Date: 20240920

ACTIVE INGREDIENTS: Human Clostridium Tetani Toxoid Immune Globulin 250 [iU]/1 mL
INACTIVE INGREDIENTS: Glycine; Water

Tetanus Immune Globulin (Human)
HyperTET®
250 Units

DESCRIPTION

Tetanus Immune Globulin (Human) — HyperTET® is a clear or slightly opalescent, and colorless or pale yellow sterile solution of human tetanus immune globulin for intramuscular administration. HyperTET contains no preservative. HyperTET is prepared from pools of human plasma collected from healthy donors by a combination of cold ethanol fractionation, caprylate precipitation and filtration, caprylate incubation, anion exchange chromatography, nanofiltration and low pH incubation. HyperTET consists of a 15% to 18% protein solution at a pH of 4.1 to 4.8 in 0.16 M to 0.26 M glycine. The product is standardized against the U.S. Standard Antitoxin and the U.S. Control Tetanus Toxin and contains not less than 250 tetanus antitoxin units per 1 mL.

When medicinal biological products are administered, the risk of infectious diseases due to transmission of pathogens cannot be totally excluded. However, in the case of products prepared from human plasma, the risk of transmission of pathogens is reduced by epidemiological surveillance of the donor population and selection of individual donors by medical interview; testing of individual donations and plasma pools; and the presence in the manufacturing processes of steps with demonstrated capacity to inactivate/remove pathogen.

In the manufacturing process of HyperTET, there are several steps with the capacity for viral inactivation or removal.(1) The main steps of the manufacturing process that contribute to the virus clearance capacity are as follows:

- Caprylate precipitation/depth filtration
- Caprylate incubation
- Depth filtration
- Column chromatography
- Nanofiltration
- Low pH final container incubation

To provide additional assurance of the pathogen safety of the final product, the capacity of the HyperTET manufacturing process to remove and/or inactivate viruses has been demonstrated by laboratory spiking studies on a scaled down process model using a wide range of viruses with diverse physicochemical properties.

The caprylate/chromatography manufacturing process was also investigated for its capacity to decrease the infectivity of an experimental agent of transmissible spongiform encephalopathy (TSE), considered as a model for the variant Creutzfeldt-Jakob disease (vCJD), and Creutzfeldt-Jakob disease (CJD) agents.(1) These studies provide reasonable assurance that low levels of vCJD/CJD agent infectivity, if present in the starting material, would be removed by the caprylate/chromatography manufacturing process.

CLINICAL PHARMACOLOGY

The occurrence of tetanus in the United States has decreased dramatically from 560 reported cases in 1947, when national reporting began, to a record low of 48 reported cases in 1987.(2) The decline has resulted from widespread use of tetanus toxoid and improved wound management, including use of tetanus prophylaxis in emergency rooms.(3)

HyperTET supplies passive immunity to those individuals who have low or no immunity to the toxin produced by the tetanus organism, Clostridium tetani. The antibodies act to neutralize the free form of the powerful exotoxin produced by this bacterium. Historically, such passive protection was provided by antitoxin derived from equine or bovine serum; however, the foreign protein in these heterologous products often produced severe allergic manifestations, even in individuals who demonstrated negative skin and/or conjunctival tests prior to administration. Estimates of the frequency of these foreign protein reactions following antitoxin of equine origin varied from 5%–30%.(4-7) If passive immunization is needed, human tetanus immune globulin (TIG) is the product of choice. It provides protection longer than antitoxin of animal origin and causes few adverse reactions.(3)

Several studies suggest the value of human tetanus antitoxin in the treatment of active tetanus.(8,9) In 1961 and 1962, Nation et al,(8) using Hyper-Tet treated 20 patients with tetanus using single doses of 3,000 to 6,000 antitoxin units in combination with other accepted clinical and nursing procedures. Six patients, all over 45 years of age, died of causes other than tetanus. The authors felt that the mortality rate (30%) compared favorably with their previous experience using equine antitoxin in larger doses and that the results were much better than the 60% national death rate for tetanus reported from 1951 to 1954.(10) Blake et al,(11) however, found in a data analysis of 545 cases of tetanus reported to the Centers for Disease Control from 1965 to 1971 that survival was no better with 8,000 units of TIG than with 500 units; however, an optimal dose could not be determined.

Serologic tests indicate that naturally acquired immunity to tetanus toxin does not occur in the United States. Thus, universal primary vaccination, with subsequent maintenance of adequate antitoxin levels by means of appropriately timed boosters, is necessary to protect persons among all age groups. Tetanus toxoid is a highly effective antigen; a completed primary series generally induces protective levels of serum antitoxin that persist for ≥10 years.(3)

Passive immunization with HyperTET may be undertaken concomitantly with active immunization using tetanus toxoid in those persons who must receive an immediate injection of tetanus antitoxin and in whom it is desirable to begin the process of active immunization. Based on the work of Rubbo,(12) McComb and Dwyer,(13) and Levine et al,(14) the physician may thus supply immediate passive protection against tetanus, and at the same time begin formation of active immunization in the injured individual which upon completion of a full toxoid series will preclude future need for antitoxin.

Peak blood levels of IgG are obtained approximately 2 days after intramuscular injection. The half-life of IgG in the circulation of individuals with normal IgG levels is approximately 23 days.(15)

In a clinical study in 12 healthy human adults receiving another hyperimmune immune globulin product, Rabies Immune Globulin (Human), HyperRAB® , prepared by the same manufacturing process, detectable passive antibody titers were observed in the serum of all subjects by 24 hours post injection and persisted through the 21 day study period.

INDICATIONS AND USAGE

HyperTET is indicated for prophylaxis against tetanus following injury in patients whose immunization is incomplete or uncertain (see below). It is also indicated, although evidence of effectiveness is limited, in the regimen of treatment of active cases of tetanus.(8,9,16)

A thorough attempt must be made to determine whether a patient has completed primary vaccination. Patients with unknown or uncertain previous vaccination histories should be considered to have had no previous tetanus toxoid doses. Persons who had military service since 1941 can be considered to have received at least one dose, and although most of them may have completed a primary series of tetanus toxoid, this cannot be assumed for each individual. Patients who have not completed a primary series may require tetanus toxoid and passive immunization at the time of wound cleaning and debridement.(3)

The following table is a summary guide to tetanus prophylaxis in wound management:

Guide to Tetanus Prophylaxis in Wound Management(3)
History of Tetanus Immunization (Doses) | Clean, Minor Wounds |  | All Other Wounds [Such as, but not limited to, wounds contaminated with dirt, feces, soil, and saliva; puncture wounds; avulsions; and wounds resulting from missiles, crushing, burns and frostbite.]
History of Tetanus Immunization (Doses) | Td [Adult type tetanus and diphtheria toxoids. If the patient is less than 7 years old, DT or DTP is preferred to tetanus toxoid alone. For persons ≥7 years of age, Td is preferred to tetanus toxoid alone. (see Dosage and Administration)] | TIG [Tetanus Immune Globulin (Human).] | Td | TIG
Uncertain or less than 3 | Yes | No | Yes | Yes
3 or more [If only three doses of fluid tetanus toxoid have been received, a fourth dose of toxoid, preferably an adsorbed toxoid, should be given.] | No [Yes if more than 10 years since the last dose.] | No | No [Yes if more than 5 years since the last dose. (More frequent boosters are not needed and can accentuate side effects).] | No

CONTRAINDICATIONS

None known.

WARNINGS

HyperTET is made from human plasma. Products made from human plasma may contain infectious agents, such as viruses, and, theoretically, the Creutzfeldt-Jakob Disease (CJD) agent that can cause disease. The risk that such products will transmit an infectious agent has been reduced by screening plasma donors for prior exposure to certain viruses, by testing for the presence of certain current virus infections, and by inactivating and/or removing certain viruses. Despite these measures, such products can still potentially transmit disease. There is also the possibility that unknown infectious agents may be present in such products. Individuals who receive infusions of blood or plasma products may develop signs and/or symptoms of some viral infections, particularly hepatitis C. ALL infections thought by a physician possibly to have been transmitted by this product should be reported by the physician or other healthcare provider to Grifols Therapeutics LLC [1-800-520-2807].

The physician should discuss the risks and benefits of this product with the patient, before prescribing or administering it to the patient.

HyperTET should be given with caution to patients with a history of prior systemic allergic reactions following the administration of human immunoglobulin preparations.

In patients who have severe thrombocytopenia or any coagulation disorder that would contraindicate intramuscular injections, HyperTET should be given only if the expected benefits outweigh the risks.

PRECAUTIONS

General

HyperTET should not be given intravenously. Intravenous injection of immunoglobulin intended for intramuscular use can, on occasion, cause a precipitous fall in blood pressure, and a picture not unlike anaphylaxis. Injections should only be made intramuscularly and care should be taken to draw back on the plunger of the syringe before injection in order to be certain that the needle is not in a blood vessel. Intramuscular injections are preferably administered in the deltoid muscle of the upper arm or lateral thigh muscle. The gluteal region should not be used as an injection site because of the risk of injury to the sciatic nerve.(17)

Chemoprophylaxis against tetanus is neither practical nor useful in managing wounds. Wound cleaning, debridement when indicated, and proper immunization are important. The need for tetanus toxoid (active immunization), with or without TIG (passive immunization), depends on both the condition of the wound and the patient’s vaccination history. Rarely has tetanus occurred among persons with documentation of having received a primary series of toxoid injections.(3) See table under See table under INDICATIONS AND USAGE.

Skin tests should not be done. The intradermal injection of concentrated IgG solutions often causes a localized area of inflammation which can be misinterpreted as a positive allergic reaction. In actuality, this does not represent an allergy; rather, it is localized tissue irritation. Misinterpretation of the results of such tests can lead the physician to withhold needed human antitoxin from a patient who is not actually allergic to this material. True allergic responses to human IgG given in the prescribed intramuscular manner are rare.

Although systemic reactions to human immunoglobulin preparations are rare, epinephrine should be available for treatment of acute anaphylactic reactions.

Drug Interactions

Antibodies in immunoglobulin preparations may interfere with the response to live viral vaccines such as measles, mumps, polio, and rubella. Therefore, use of such vaccines should be deferred until approximately 3 months after Tetanus Immune Globulin (Human) — HyperTET® administration.

No interactions with other products are known.

Pregnancy

Animal reproduction studies have not been conducted with HyperTET. It is also not known whether HyperTET can cause fetal harm when administered to a pregnant woman or can affect reproduction capacity. HyperTET should be given to a pregnant woman only if clearly needed.

Pediatric Use

Safety and effectiveness in the pediatric population have not been established.

ADVERSE REACTIONS

Slight soreness at the site of injection and slight temperature elevation may be noted at times. Sensitization to repeated injections of human immunoglobulin is extremely rare.

In the course of routine injections of large numbers of persons with immunoglobulin there have been a few isolated occurrences of angioneurotic edema, nephrotic syndrome, and anaphylactic shock after injection.

OVERDOSAGE

Although no data are available, clinical experience with other immunoglobulin preparations suggests that the only manifestations would be pain and tenderness at the injection site.

DOSAGE AND ADMINISTRATION

Routine prophylactic dosage schedule:

Adults and children 7 years and older: HyperTET, 250 units should be given by deep intramuscular injection (see PRECAUTIONS). At the same time, but in a different extremity and with a separate syringe, Tetanus and Diphtheria Toxoids Adsorbed (For Adult Use) (Td) should be administered according to the manufacturer's package insert. Adults with uncertain histories of a complete primary vaccination series should receive a primary series using the combined Td toxoid. To ensure continued protection, booster doses of Td should be given every 10 years. (3)
Children less than 7 years old: In small children the routine prophylactic dose of HyperTET may be calculated by the body weight (4.0 units/kg). However, it may be advisable to administer the entire contents of the syringe of HyperTET (250 units) regardless of the child's size, since theoretically the same amount of toxin will be produced in the child's body by the infecting tetanus organism as it will in an adult's body. At the same time but in a different extremity and with a different syringe, Diphtheria and Tetanus Toxoids and Pertussis Vaccine Adsorbed (DTP) or Diphtheria and Tetanus Toxoids Adsorbed (For Pediatric Use) (DT), if pertussis vaccine is contraindicated, should be administered per the manufacturer's package insert.
Note: The single injection of tetanus toxoid only initiates the series for producing active immunity in the recipient. The physician must impress upon the patient the need for further toxoid injections in 1 month and 1 year. Without such, the active immunization series is incomplete. If a contraindication to using tetanus toxoid-containing preparations exists for a person who has not completed a primary series of tetanus toxoid immunization and that person has a wound that is neither clean nor minor, only passive immunization should be given using tetanus immune globulin.(3) See table under INDICATIONS AND USAGE.
Available evidence indicates that complete primary vaccination with tetanus toxoid provides long lasting protection ≥10 years for most recipients. Consequently, after complete primary tetanus vaccination, boosters-even for wound management-need be given only every 10 years when wounds are minor and uncontaminated. For other wounds, a booster is appropriate if the patient has not received tetanus toxoid within the preceding 5 years. Persons who have received at least two doses of tetanus toxoid rapidly develop antibodies. (3) The prophylactic dosage schedule for these patients and for those with incomplete or uncertain immunity is shown on the table in INDICATIONS AND USAGE.
Since tetanus is actually a local infection, proper initial wound care is of paramount importance. The use of antitoxin is adjunctive to this procedure. However, in approximately 10% of recent tetanus cases, no wound or other breach in skin or mucous membrane could be implicated. (18)

Treatment of active cases of tetanus:

Standard therapy for the treatment of active tetanus including the use of HyperTET must be implemented immediately. The dosage should be adjusted according to the severity of the infection. (8,9)

Parenteral drug products should be inspected visually for particulate matter and discoloration prior to administration, whenever solution and container permit. They should not be used if particulate matter and/or discoloration are present.

HyperTET is supplied with a syringe and an attached UltraSafe® Needle Guard for your protection and convenience. Please follow instructions below for proper use of syringe and UltraSafe® Needle Guard.

Directions for Syringe Usage

1. Remove the prefilled syringe from the package. Lift syringe by barrel, not by plunger.
2. Twist the plunger rod clockwise until the threads are seated.
3. With the needle shield secured on the syringe tip, push the plunger rod forward a few millimeters to break any friction seal between the stopper and the glass syringe barrel.
4. Remove the needle shield and expel air bubbles. [Do not remove the needle shield to prepare the product for administration until immediately prior to the anticipated injection time.]
5. Proceed with hypodermic needle puncture.
6. Aspirate prior to injection to confirm that the needle is not in a vein or artery.
7. Inject the medication.
8. Keeping your hands behind the needle, grasp the guard with free hand and slide forward toward needle until it is completely covered and guard clicks into place. If audible click is not heard, guard may not be completely activated. (See Diagrams A and B)
9. Place entire prefilled glass syringe with guard activated into an approved sharps container for proper disposal. (See Diagram C)

A number of factors could reduce the efficacy of this product or even result in an ill effect following its use. These include improper storage and handling of the product after it leaves our hands, diagnosis, dosage, method of administration, and biological differences in individual patients. Because of these factors it is important that this product be stored properly and that the directions be followed carefully during use.

HOW SUPPLIED

HyperTET is supplied in 250 unit prefilled disposable syringes with attached needles.
HyperTET contains no preservative and is not made with natural rubber latex.

NDC Number | Size
13533-634-02 | 250 unit syringe

STORAGE

Store at 2–8°C (36–46°F). Solution that has been frozen should not be used. Discard unused portion.

CAUTION

Rx only

U.S. federal law prohibits dispensing without prescription.

REFERENCES

1. Barnette D, Roth NJ, Hotta J, et al. Pathogen safety profile of a 10% IgG preparation manufactured using a depth filtration-modified process. Biologicals 2012;40:247-53.
2. Tetanus — United States, 1987 and 1988, MMWR 39(3): 37-41, 1990.
3. Diphtheria, Tetanus, and Pertussis: Recommendations for Vaccine Use and Other Preventive Measures. Recommendations of the Immunization Practices Advisory Committee (ACIP). MMWR 40 (RR-10): 1-28, 1991.
4. Moynihan NH: Tetanus prophylaxis and serum sensitivity tests. Br Med J 1:260-4, 1956.
5. Scheibel I: The uses and results of active tetanus immunization. Bull WHO 13:381-94, 1955.
6. Edsall G: Specific prophylaxis of tetanus. JAMA 171(4):417-27, 1959.
7. Bardenwerper HW: Serum neuritis from tetanus antitoxin. JAMA 179(10):763-6, 1962.
8. Nation NS, Pierce NF, Adler SJ, et al: Tetanus: the use of human hyperimmune globulin in treatment. Calif Med 98(6):305-6, 1963.
9. Ellis M: Human antitetanus serum in the treatment of tetanus. Br Med J 1(5338):1123-6, 1963.
10. Axnick NW, Alexander ER: Tetanus in the United States: A review of the problem. Am J Public Health 47(12):1493-1501, 1957.
11. Blake PA, Feldman RA, Buchanan TM, et al: Serologic therapy of tetanus in the United States, 1965-1971. JAMA 235(1):42-4, 1976.
12. Rubbo SD: New approaches to tetanus prophylaxis. Lancet 2(7461):449-53, 1966.
13. McComb JA, Dwyer RC: Passive-active immunization with tetanus immune globulin (human). N Engl J Med 268(16):857-62, 1963.
14. Levine L, McComb JA, Dwyer RC, et al: Active-passive tetanus immunization; choice of toxoid, dose of tetanus immune globulin and timing of injections. N Engl J Med 274(4):186-90, 1966.
15. Waldmann TA, Strober W, Blaese RM: Variations in the metabolism of immunoglobulins measured by turnover rates. In Merler E (ed.): Immunoglobulins: biologic aspects and clinical uses. Washington, DC, Nat Acad Sci, 1970, p. 33-51.
16. McCracken GH Jr., Dowell DL, Marshall FN: Double-blind trial of equine antitoxin and human immune globulin in tetanus neonatorum. Lancet 1(7710):1146-9, 1971.
17. Recommendations of the Advisory Committee on Immunization Practices (ACIP) and the American Academy of Family Physicians (AAFP): General recommendations on immunization. MMWR 2002: 51(RR02), 1-36.
18. Tetanus-Rates by year, United States, 1955-1984. Annual Summary 1984. MMWR 33 (54):61, 1986.

Rev. 8/2022

Grifols Therapeutics LLC
Research Triangle Park, NC 27709 USA
U.S. License No. 1871

3063801

PACKAGE LABEL

250 Units / 1 mL
Tetanus
Immune
Globulin
(Human)
HyperTET®
1 mL 1 mL
Solution for Intramuscular
Injection
250 Units / mL
Contents: One single-dose
disposable syringe with
attached needle.
Tetanus Immune Globulin
(Human) is a sterile solution
of immunoglobulin containing
15%-18% protein stabilized with
0.16 M to 0.26 M glycine.
FOR INTRAMUSCULAR
INJECTION ONLY.
DO NOT GIVE INTRAVENOUSLY.
NDC 13533-634-02
GRIFOLS
The patient and physician should
discuss the risks and benefits of this
product.
The potency of each syringe is not
less than 250 antitoxin units based on
the U.S. Standard Antitoxin and the
U.S. Control Tetanus Toxin.
For complete dosage and
administration information, read
enclosed package insert.
1 mL 1 mL
For directions for syringe usage, see
enclosed package insert.
Store at 2°C to 8°C (36°F to 46°F).
Do not freeze.
Do not use if the syringe is prematurely
engaged.
Not returnable for credit or
exchange.
Rx only
Not made with natural rubber latex.
No preservative
Discard unused portion.
Grifols Therapeutics LLC
Research Triangle Park,
NC 27709 USA
U.S. License No. 1871
GRIFOLS
Carton: 3060175
NDC 13533-634-02 GTIN 00313533634025
LOT XXXXXXXXXX
EXP DDMMMYYYY
SN XXXXXXXXXXXXXXXX
HyperTET® 250 Units / 1 mL

Tetanus Immune
Globulin (Human)
HyperTET® 250 Units / 1 mL
One 1 mL Single Dose
The patient and physician should discuss
the risks and benefits of this product.
Grifols Therapeutics LLC
RTP, NC 27709 USA
U.S. License No. 1871
3060170
Lot
Exp.